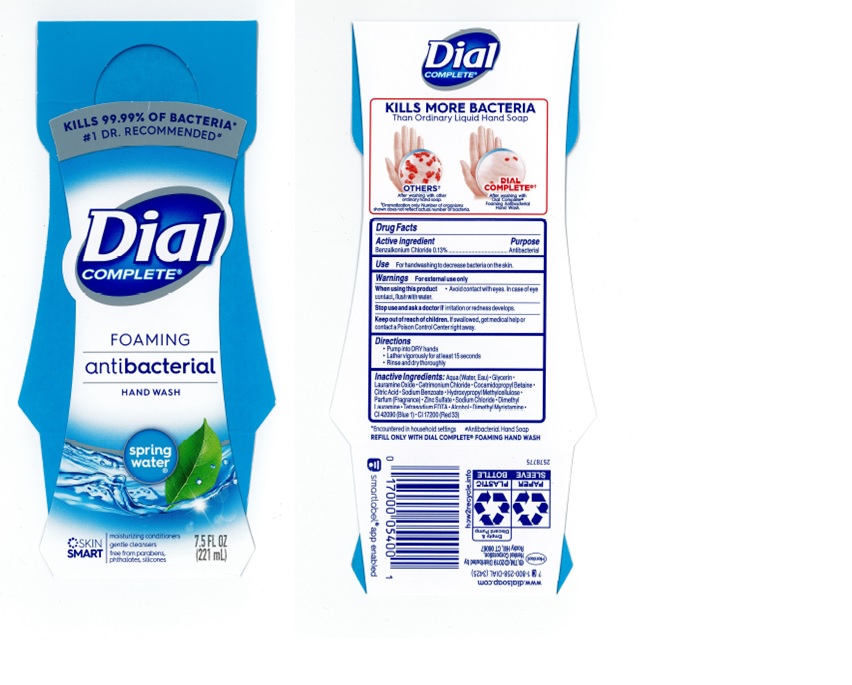 DRUG LABEL: Dial Antimicrobial
NDC: 57702-501 | Form: LIQUID
Manufacturer: Bocchi Laboratories
Category: otc | Type: HUMAN OTC DRUG LABEL
Date: 20210511

ACTIVE INGREDIENTS: BENZALKONIUM CHLORIDE 13 g/100 mL
INACTIVE INGREDIENTS: DIMETHYL LAURAMINE; ANHYDROUS CITRIC ACID; GLYCERIN; CETRIMONIUM CHLORIDE; SODIUM CHLORIDE; WATER; DIMETHYL MYRISTAMINE; SODIUM BENZOATE; ALCOHOL; LAURAMINE OXIDE; FD&C BLUE NO. 1; D&C RED NO. 33; ZINC SULFATE; HYPROMELLOSE, UNSPECIFIED; COCAMIDOPROPYL BETAINE; EDETATE SODIUM

Dial Antimicrobial

Active Ingredient
Benzalkonium Chloride 0.13%

Purpose
Antibacterial

Uses

- For handwashing to decrease bacteria on the skin

Warnings
For external use only.

Stop use and ask a doctor if

- if irritation or redness develops

Keep out of reach of children.
If swallowed, get medical help or contact a Poison Control center right away.

Directions

- Pump into dry hands.
- Lather vigorously for at least 15 seconds
- Rinse thouroughly and dry

INACTIVE INGREDIENT

Aqua (Water, Eau), Glycerin, Lauramine Oxide, Cetrimonium Chloride, Cocamidopropyl Betaine, Sodium Benzoate, Hydroxypropyl Methylcellulose, Parfum (Fragrance), Zinc Sulfate, Sodium Chloride, Dimethyl Lauramine, Tetrasodium EDTA, Alcohol, Dimethyl Myristamine, CI 42090 (Blue 1), CI 17200 (Red 33).

When using this product

Avoid contact with eyes, in case of eye contact, flush with water